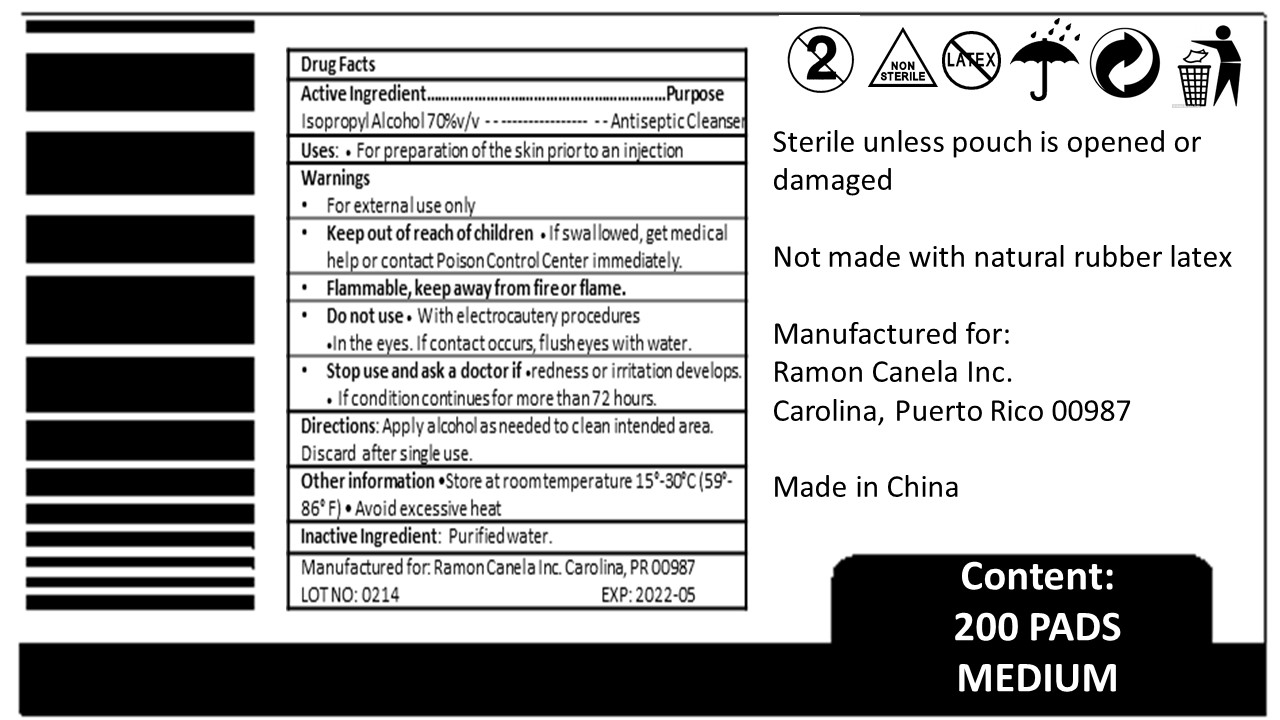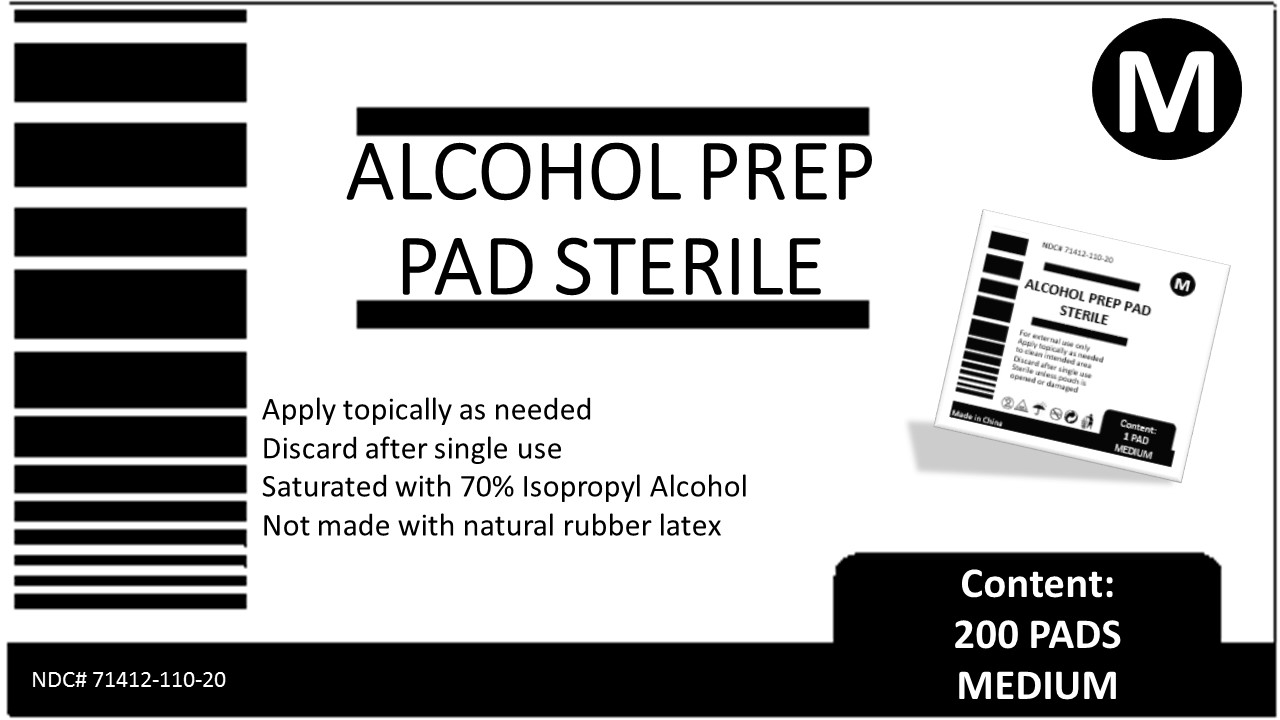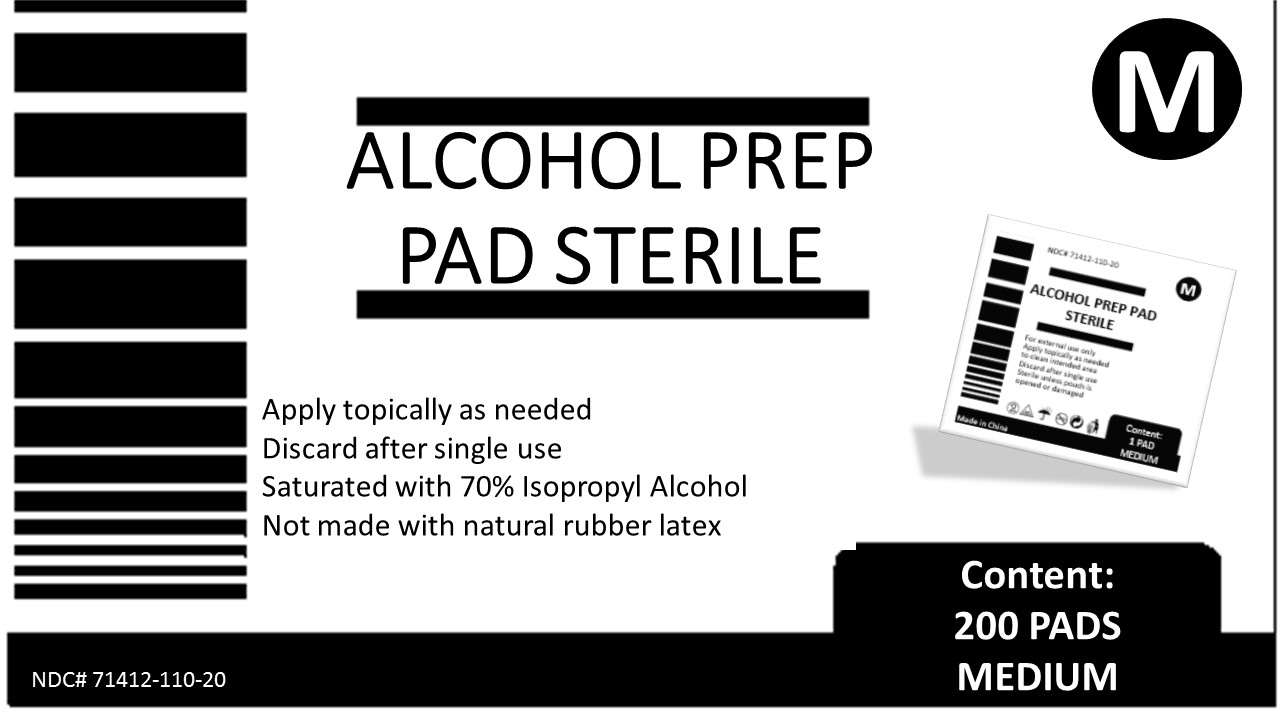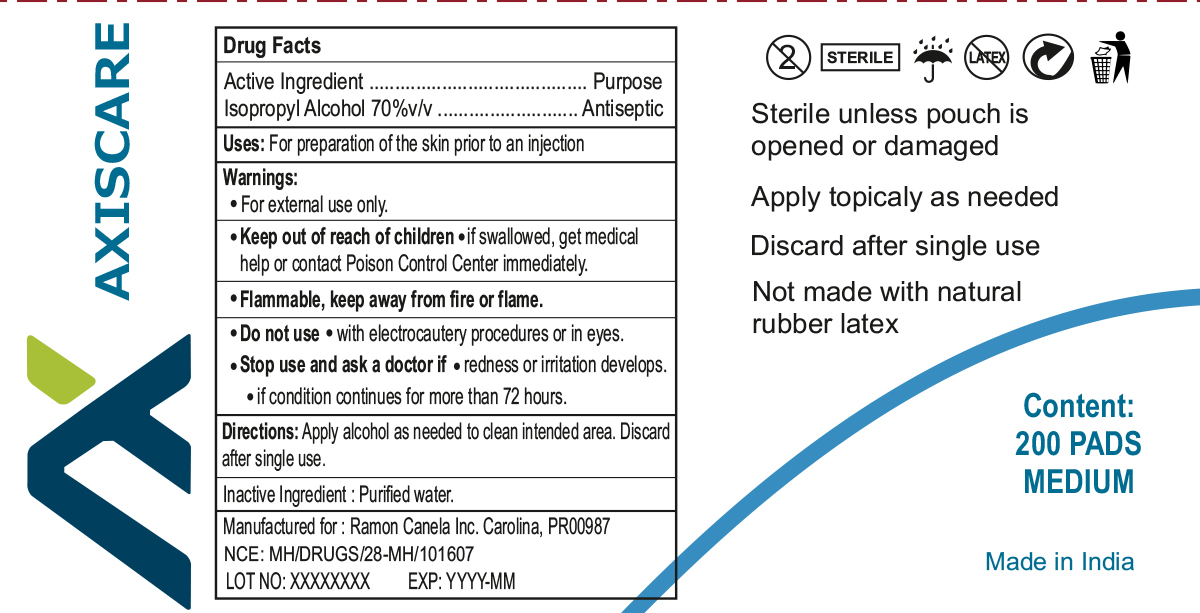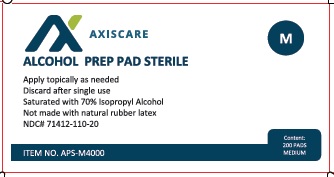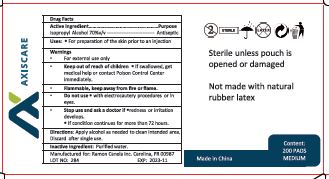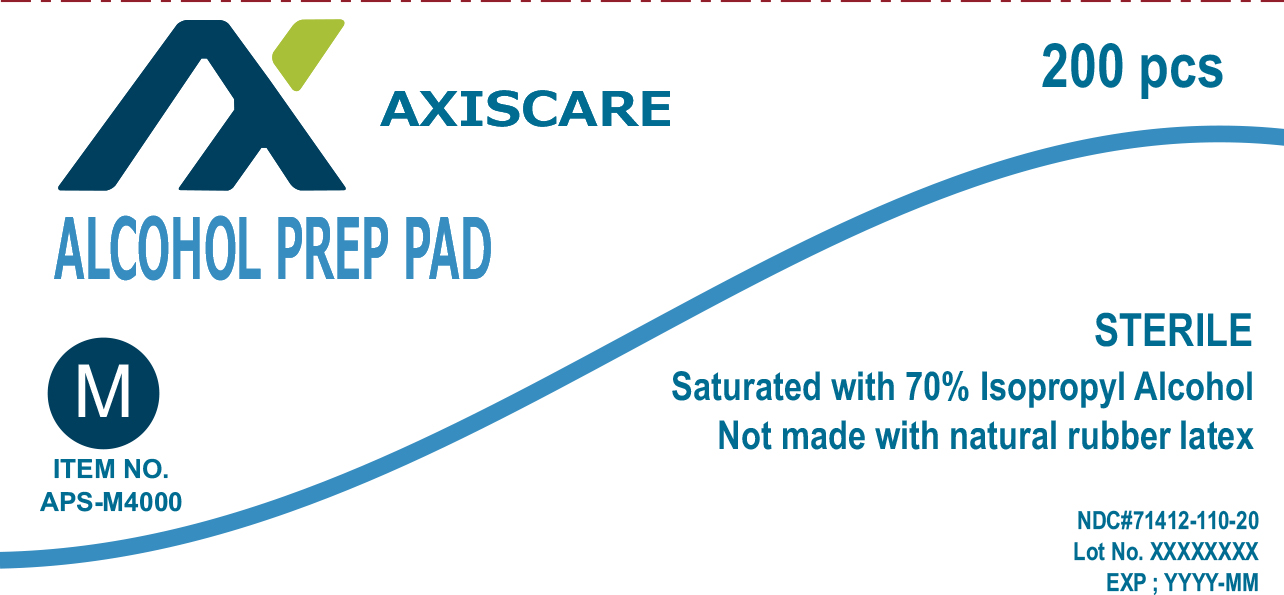 DRUG LABEL: Alcohol Prep Pad
NDC: 71412-110 | Form: SWAB
Manufacturer: R&C Imports LLC
Category: otc | Type: HUMAN OTC DRUG LABEL
Date: 20241227

ACTIVE INGREDIENTS: ISOPROPYL ALCOHOL 0.7 mL/1 1
INACTIVE INGREDIENTS: WATER

GENERAL PRECAUTIONS

Apply topically as needed

Discard after single use

Saturated with 70% Isopropyl Alcohol
Not made with natural rubber latex

Active Ingredient:

Isopropyl Alcohol 70%v/v

Purpose

Antiseptic Cleanser

Use:

For preparation of the skin prior to an injection.

Warnings

•For external use only
•Flammable, keep away from fire or flame.

Do not use

with electrocautery procedures

in the eyes. If contact occurs, flush eyes with water

Stop use and ask a doctor if

- redness or irritation develops.
- If condition continues for more than 72 hours.

Keep out of reach of children

•If swallowed, get medical help or contact Poison Control Center immediately.

Directions

Apply alcohol as needed to clean intended area.

Discard after single use.

Other Information

Store at Room Temperature 15 - 30 C (89 - 86 F)

Inactive Ingredient

Purified water.

200 Pad Medium Box

M

Alcohol Prep

Pad Sterile

Apply topically as needed

Discard after single use

Saturated with 70% Isopropyl Alcohol
Not made with natural rubber latex

Content:

200 Pad

Medium

NDC: 71412-110-20